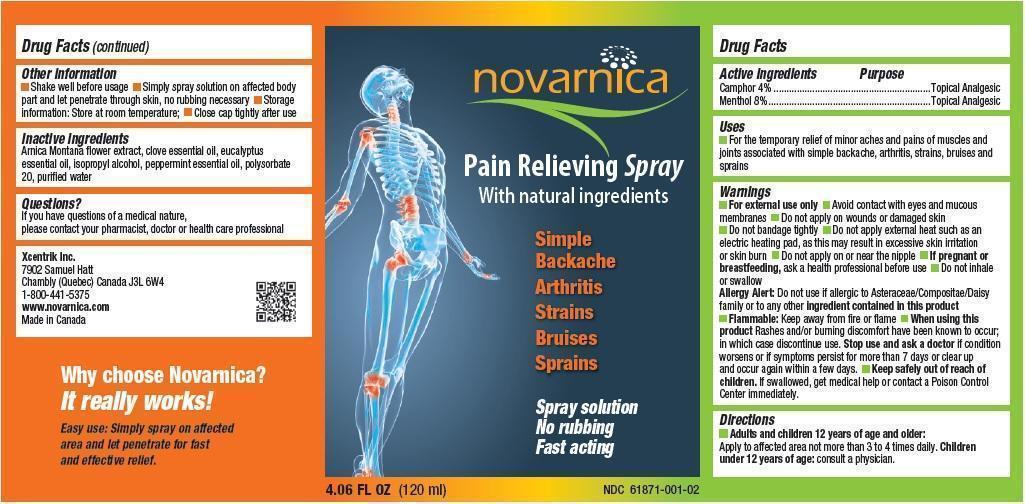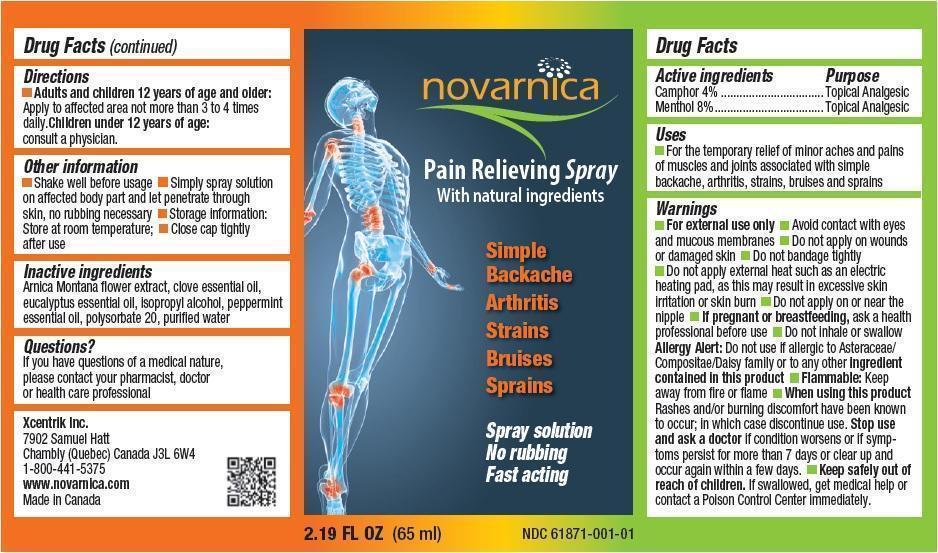 DRUG LABEL: Novarnica
NDC: 61871-001 | Form: SPRAY
Manufacturer: Xcentrik Inc.
Category: otc | Type: HUMAN OTC DRUG LABEL
Date: 20221219

ACTIVE INGREDIENTS: CAMPHOR (NATURAL) 4 g/100 mL; MENTHOL 8 g/100 mL
INACTIVE INGREDIENTS: ARNICA MONTANA FLOWER; CLOVE OIL; EUCALYPTUS OIL; ISOPROPYL ALCOHOL; PEPPERMINT OIL; POLYSORBATE 20; WATER

Drug Facts

Active ingredients

Camphor 4%
Menthol 8%

Purpose

Topical Analgesic

Uses

For the temporary relief of minor aches and pains of muscles and joints associated with simple backache, arthritis, strains, bruises and sprains

Warnings

- For external use only
- Avoid contact with eyes and mucous membranes
- Do not apply on wounds or damaged skin
- Do not bandage tightly
- Do not apply external heat such as an electric heating pad, as this may result in excessive skin irritation or skin burn
- Do not apply on or near the nipple
- If pregnant or breastfeeding, ask a health professional before use
- Do not inhale or swallow
- Allergy Alert: Do not use if allergic to Asteraceae/Compositae/Daisy family or to any other ingredient contained in this product
- Flammable: Keep away from fire or flame
- When using this product Rashes and/or burning discomfort have been known to occur; in which case discontinue use. Stop use and ask a doctor if condition worsens or if symptoms persist for more than 7 days or clear up and occur again within a few days.

KEEP OUT OF REACH OF CHILDREN

- Keep safely out of reach of children. If swallowed, get medical help or contact a Poison Control Center immediately.

Directions

- Adults and children 12 years of age and older: Apply to affected area not more than 3 to 4 times daily.
- Children under 12 years of age: consult a physician.

Other information

- Shake well before usage
- Simply spray solution on affected body part and let penetrate through skin, no rubbing necessary
- Storage information: Store at room temperature;
- Close cap tightly after use

Inactive ingredients

Arnica Montana flower extract, clove essential oil, eucalyptus essential oil, isopropyl alcohol, peppermint essential oil, polysorbate 20, purified water

Questions?

If you have questions of a medical nature, please contact your pharmacist, doctor or health care professional

Xcentrik Inc.
7902 Samuel Hatt
Chambly (Quebec) Canada J3L 6W4
1-800-441-5375
www.novarnica.com
Made in Canada

Principal Display Panel

novarnica

Pain Relieving Spray
With natural ingredients

Simple
Backache
Arthritis
Strains
Bruises
Sprains

Spray solution
No rubbing
Fast acting

2.19 FL OZ (65 ml)

PACKAGE LABEL

4.06 FL OZ (120 ml)